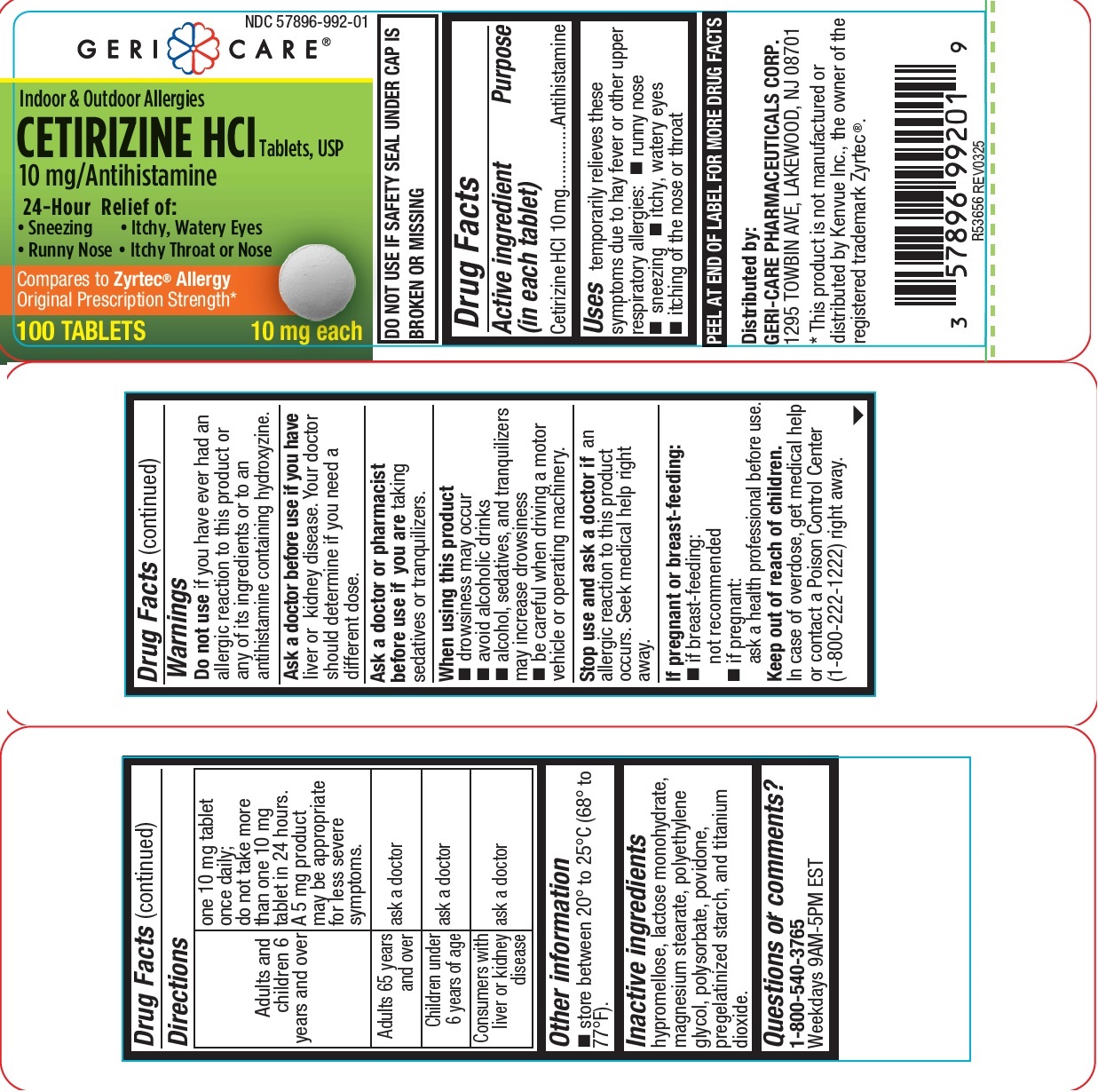 DRUG LABEL: Cetirizine HCl
NDC: 57896-992 | Form: TABLET, FILM COATED
Manufacturer: GERI-CARE PHARMACEUTICAL CORP
Category: otc | Type: HUMAN OTC DRUG LABEL
Date: 20250424

ACTIVE INGREDIENTS: CETIRIZINE HYDROCHLORIDE 10 mg/1 1
INACTIVE INGREDIENTS: STARCH, CORN; LACTOSE MONOHYDRATE; MAGNESIUM STEARATE; POLYSORBATE 80; POVIDONE, UNSPECIFIED; HYPROMELLOSE, UNSPECIFIED; TITANIUM DIOXIDE; POLYETHYLENE GLYCOL, UNSPECIFIED

992

ACTIVE INGREDIENT

Cetirizine HCl 10 mg

PURPOSE

Antihistamine

Uses

Temporarily relieves these symptoms due to hay fever or other upper respiratory allergies:

- runny nose
- sneezing,
- itchy, watery eyes
- itching of the nose or throat

Warnings

Do not use if you have ever had an allergic reaction to this product or any of its ingredients or an antihistamine containing hydroxyzine

Ask a doctor before use if you have liver or kidney disease. Your doctor should determine if you need a different dose.

Ask a doctor or pharmacist before use if you are taking sedatives or tranquilizers

When using this product

- drowsiness may occur
- Avoid alcoholic drinks
- Alcohol, sedatives and tranquilizers may increase drowsiness
- Be careful when driving a motor vehicle or operating machinery.

Stop use and ask a doctor if an allergic reaction to this product occurs. Seek medical help right away.

If pregnant or breast-feeding:

- if breast-feeding: not recommended
- if pregnant: ask a health professional before use.

Keep out of reach of children. In case of overdose, get medical help or contact a Poison Control Center (1-800-222-1222) right away.

DOSAGE AND ADMINISTRATION

Adults and children 6 years and over | one 10 mg tablet once daily; do not take more than one 10 mg tablet in 24 hours. A 5 mg product may be appropriate for less severe symptoms.
Adults 65 years and over | ask a doctor
Children under 6 years of age | ask a doctor
Consumers with liver or kidney disease | ask a doctor

Other information

store between 20° to 25°C (68° to 77°F).

INACTIVE INGREDIENT

hypromellose, lactose monohydrate, magnesium stearate, polyethylene glycol, polysorbate, povidone,
pregelatinized starch, and titanium dioxide.

Questions or comments?

1-800-540-3765
Weekdays 9AM-5PM EST